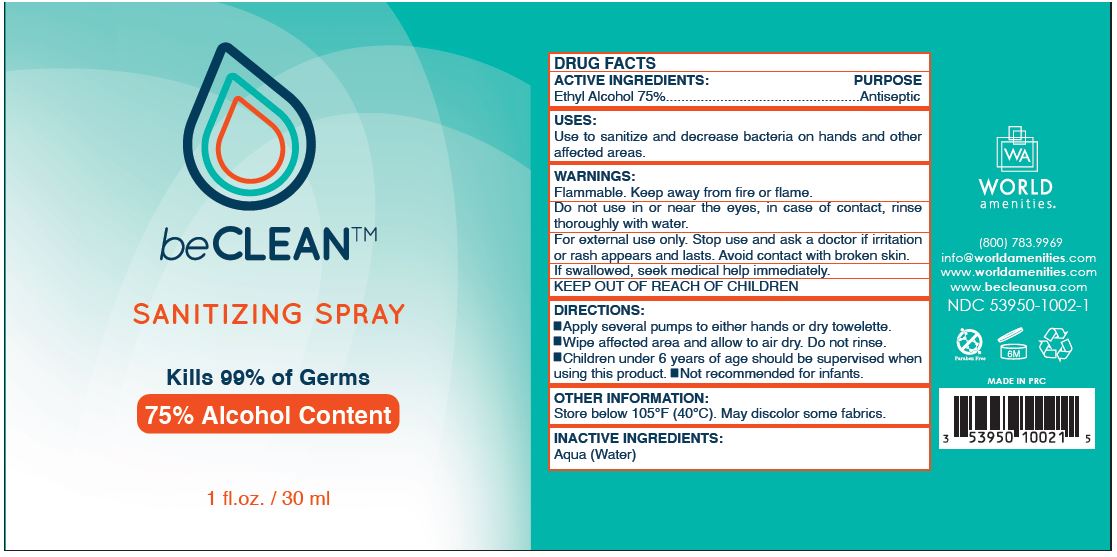 DRUG LABEL: beCLEAN HAND SANITIZER
NDC: 53950-1002 | Form: SPRAY
Manufacturer: World Amenities
Category: otc | Type: HUMAN OTC DRUG LABEL
Date: 20201213

ACTIVE INGREDIENTS: ALCOHOL 75 mL/100 mL
INACTIVE INGREDIENTS: WATER

beCLEAN SANITIZING SPRAY, 75% ALCOHOL CONTENT

ACTIVE INGREDIENT

ETHYL ALCOHOL 75%

PURPOSE

ANTISEPTIC

USES

FOR HAND SANITIZING TO DECREASE BACTERIA ON THE SKIN. RECOMMENDED FOR REPEATED USE.

WARNINGS

Flammable. Keep away from fire or flame.

Do not use in or near the eyes, in case of contact, rinse thoroughly with water.

For external use only. Stop use and ask a doctor if irritation or rash appears and lasts. Avoid contact with broken skin.

If swallowed, seek medical help immediately.

Keep out of reach of children.

DIRECTIONS

- Apply enough product to cover hands thoroughly.
- Rub hands together, until hands feel dry. Do not rinse.
- Children under 6 years of age should be supervised when using this product.
- Not recommended for infants.

OTHER INFORMATION

Store below 105°F (40°C). May discolor some fabrics.

INACTIVE INGREDIENTS

Aqua (Water)